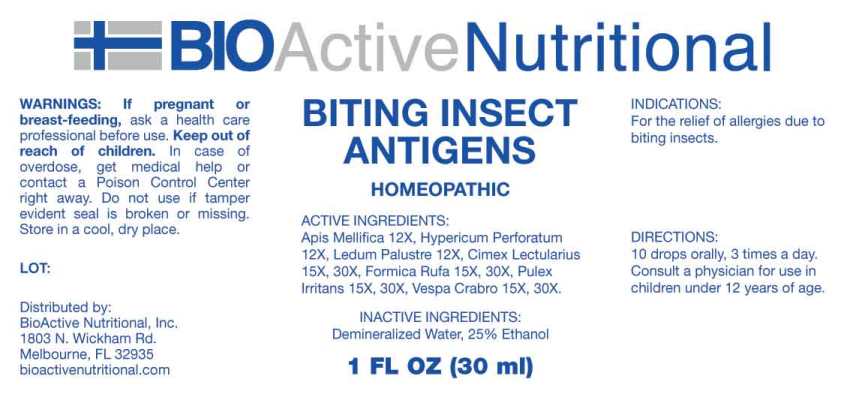 DRUG LABEL: Biting Insect Antigens
NDC: 43857-0263 | Form: LIQUID
Manufacturer: BioActive Nutritional, Inc.
Category: homeopathic | Type: HUMAN OTC DRUG LABEL
Date: 20230607

ACTIVE INGREDIENTS: APIS MELLIFERA 12 [hp_X]/1 mL; HYPERICUM PERFORATUM WHOLE 12 [hp_X]/1 mL; RHODODENDRON TOMENTOSUM LEAFY TWIG 12 [hp_X]/1 mL; CIMEX LECTULARIUS 15 [hp_X]/1 mL; FORMICA RUFA 15 [hp_X]/1 mL; PULEX IRRITANS 15 [hp_X]/1 mL; VESPA CRABRO 15 [hp_X]/1 mL
INACTIVE INGREDIENTS: WATER; ALCOHOL

Drug Facts

ACTIVE INGREDIENTS:

Apis Mellifica 12X, Hypericum Perforatum 12X, Ledum Palustre 12X, Cimex Lectularius (Bed Bug) 15X, 30X, Formica Rufa (Red Wood Ants) 15X, 30X, Pulex Irritans (Human Flea) 15X, 30X, Vespa Crabro (Hornet, Wasp) 15X, 30X.

INDICATIONS:

For the relief of allergies due to biting insects.

WARNINGS:

If pregnant or breast-feeding, ask a health care professional before use.

Keep out of reach of children. In case of overdose, get medical help or contact a Poison Control Center right away.

Do not use if tamper evident seal is broken or missing.

Store in a cool, dry place.

Keep out of reach of children. In case of overdose, get medical help or contact a Poison Control Center right away.

DIRECTIONS:

10 drops orally, 3 times a day. Consult a physician for use in children under 12 years of age.

INDICATIONS:

For the relief of allergies due to biting insects.

INACTIVE INGREDIENTS:

Demineralized Water, 25% Ethanol.

QUESTIONS:

Distributed by:
BioActive Nutritional, Inc.
1803 N. Wickham Rd.
Melbourne, FL 32935
bioactivenutritional.com

PACKAGE LABEL DISPLAY:

BIOActive Nutritional

BITING INSECT ANTIGENS

HOMEOPATHIC

1 FL OZ (30 ml)